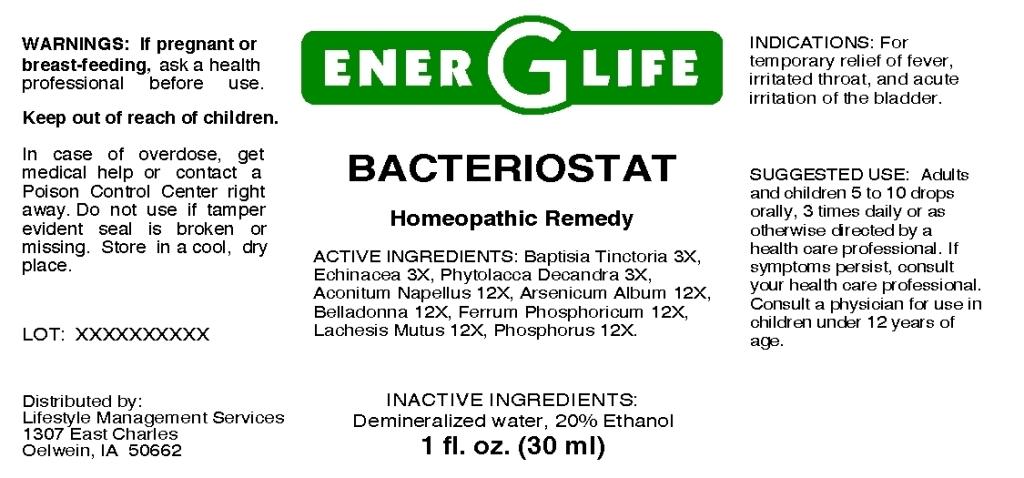 DRUG LABEL: Bacteriostat
NDC: 57520-0656 | Form: LIQUID
Manufacturer: Apotheca Company
Category: homeopathic | Type: HUMAN OTC DRUG LABEL
Date: 20110330

ACTIVE INGREDIENTS: BAPTISIA TINCTORIA ROOT 3 [hp_X]/1 mL; ECHINACEA 3 [hp_X]/1 mL; PHYTOLACCA AMERICANA ROOT 3 [hp_X]/1 mL; ACONITUM NAPELLUS 12 [hp_X]/1 mL; ARSENIC TRIOXIDE 12 [hp_X]/1 mL; ATROPA BELLADONNA 12 [hp_X]/1 mL; FERRUM PHOSPHORICUM 12 [hp_X]/1 mL; LACHESIS MUTA VENOM 12 [hp_X]/1 mL; PHOSPHORUS 12 [hp_X]/1 mL
INACTIVE INGREDIENTS: WATER; ALCOHOL

Bacteriostat

ACTIVE INGREDIENT

ACTIVE INGREDIENTS: Baptisia tinctoria 3X, Echinacea 3X, Phytolacca decandra 3X, Aconitum napellus 12X, Arsenicum album 12X, Belladonna 12X, Ferrum phosphoricum 12X, Lachesis mutus 12X, Phosphorus 12X.

PURPOSE

INDICATIONS: For temporary relief of fever, irritated throat, and acute irritation of the bladder.

WARNINGS

WARNINGS: If pregnant or breast-feeding, ask a health professional before use.

Keep out of reach of children. In case of overdose, get medical help or contact a Poison Control Center right away.

Do not use if tamper evident seal is broken or missing. Store in a cool, dry place.

DOSAGE AND ADMINISTRATION

SUGGESTED USE: Adults and children 5 to 10 drops orally, 3 times daily or as otherwise directed by a health care professional. If symptoms persist, Consult your health care professional. Consult a physician for use in children under 12 years of age.

INACTIVE INGREDIENTS: Demineralized water, 20% Ethanol.

KEEP OUT OF REACH OF CHILDREN. In case of overdose, get medical help or contact a Poison Control Center right away.

INDICATIONS AND USAGE

INDICATIONS: For temporary relief of fever, irritated throat, and acute irritation of the bladder.

QUESTIONS

Distributed by:

Lifestyle Management Services

1307 East Charles

Oelwein, IA 50662

PACKAGE LABEL

ENER G LIFE

BACTERIOSTAT

Homeopathic Remedy

1 fl. oz (30 ml)